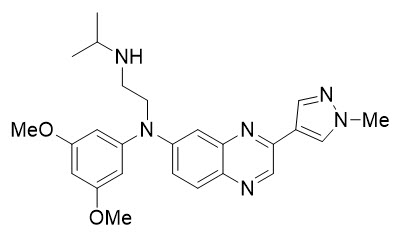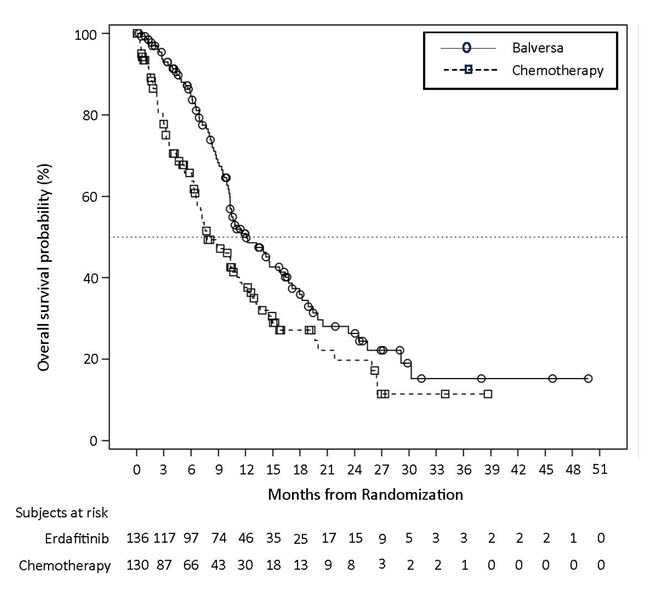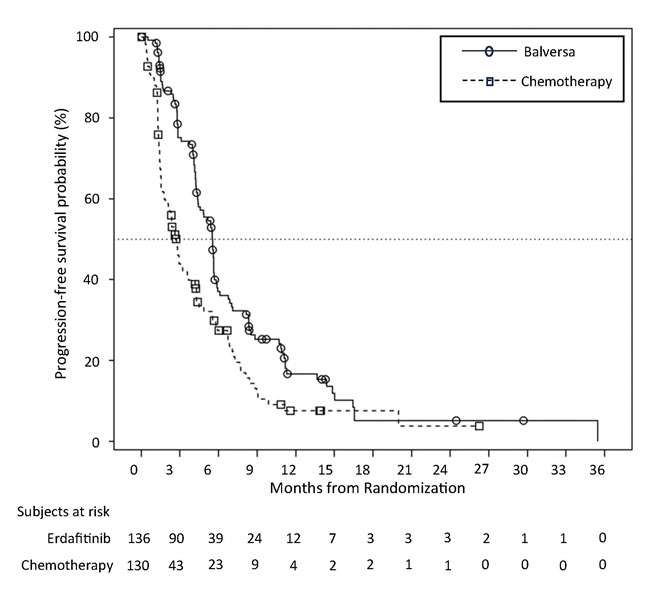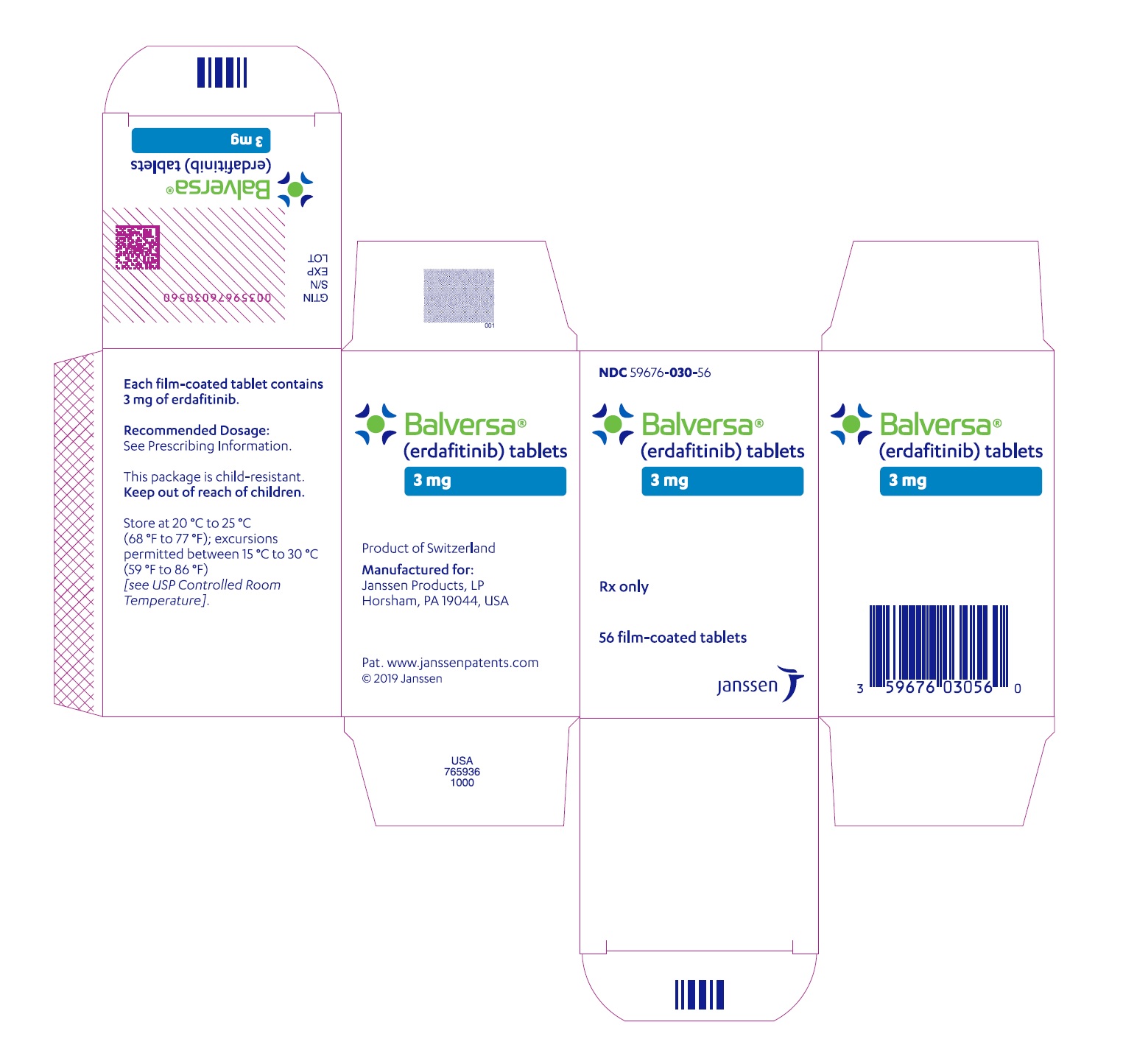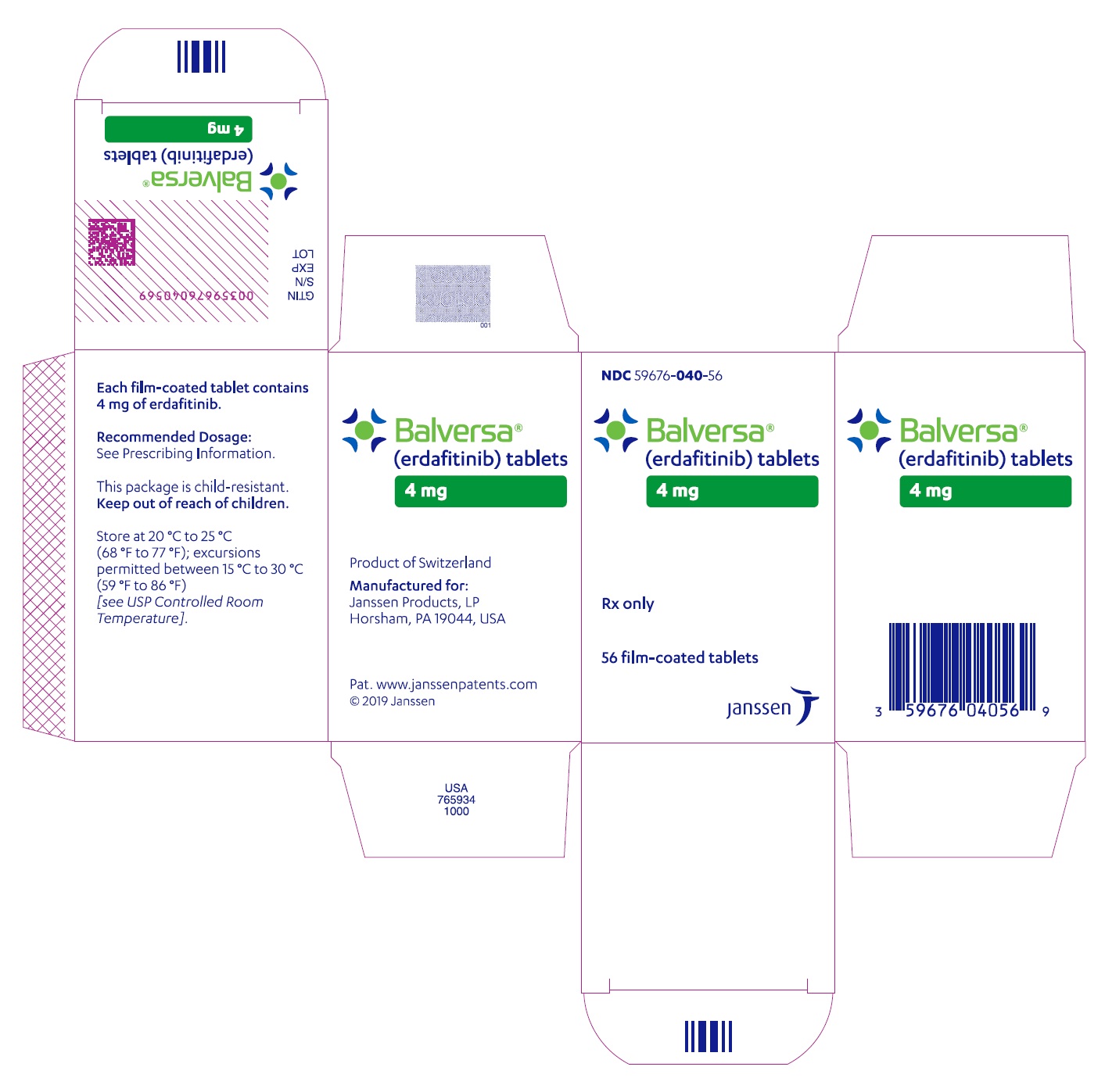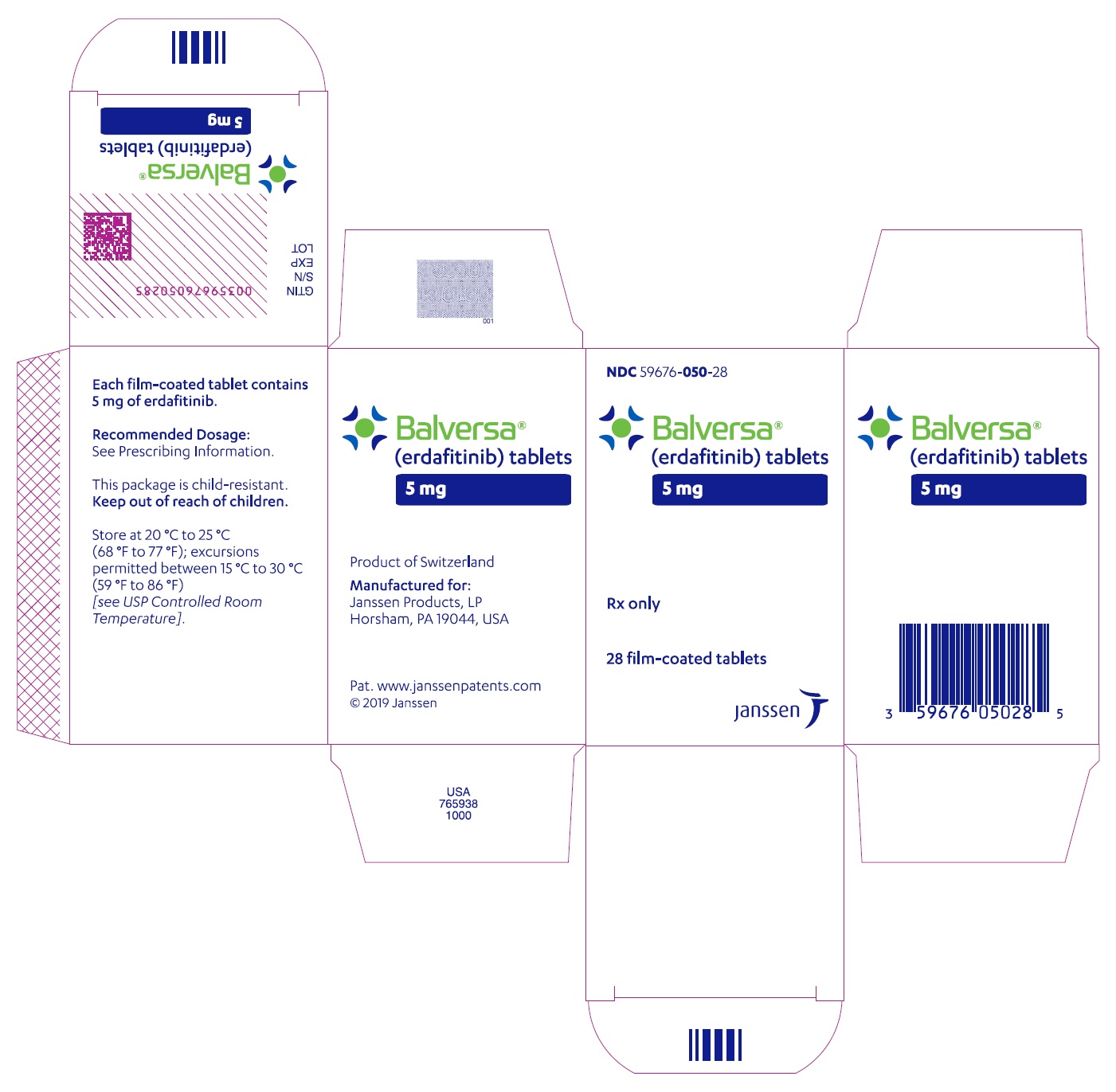 DRUG LABEL: BALVERSA
NDC: 59676-040 | Form: TABLET, FILM COATED
Manufacturer: Janssen Products LP
Category: prescription | Type: HUMAN PRESCRIPTION DRUG LABEL
Date: 20251024

ACTIVE INGREDIENTS: ERDAFITINIB 4 mg/1 1
INACTIVE INGREDIENTS: CROSCARMELLOSE SODIUM; MAGNESIUM STEARATE; MANNITOL; MEGLUMINE; MICROCRYSTALLINE CELLULOSE; GLYCERYL MONOCAPRYLOCAPRATE; POLYVINYL ALCOHOL, UNSPECIFIED; SODIUM LAURYL SULFATE; TALC; TITANIUM DIOXIDE; FERRIC OXIDE YELLOW; FERRIC OXIDE RED

HIGHLIGHTS OF PRESCRIBING INFORMATION

These highlights do not include all the information needed to use BALVERSA safely and effectively. See full prescribing information for BALVERSA.
BALVERSA®(erdafitinib) tablets, for oral use
Initial U.S. Approval: 2019

1 INDICATIONS AND USAGE

BALVERSA is a kinase inhibitor indicated for the treatment of adult patients with locally advanced or metastatic urothelial carcinoma (mUC) with susceptible FGFR3 genetic alterations whose disease has progressed on or after at least one line of prior systemic therapy.

Select patients for therapy based on an FDA-approved companion diagnostic for BALVERSA. (1, 2.1)

Limitations of Use

BALVERSA is not recommended for the treatment of patients who are eligible for and have not received prior PD-1 or PD-L1 inhibitor therapy. (1, 14.1)

2 DOSAGE AND ADMINISTRATION

- Confirm the presence of FGFR3genetic alterations in tumor specimens prior to initiation of treatment with BALVERSA. (2.1)
- Recommended initial dosage: 8 mg orally once daily with a dose increase to 9 mg daily if criteria are met. (2.2)
- Swallow whole with or without food. (2.2)

3 DOSAGE FORMS AND STRENGTHS

Tablets: 3 mg, 4 mg, and 5 mg. (3)

4 CONTRAINDICATIONS

None. (4)

5 WARNINGS AND PRECAUTIONS

- Ocular disorders: BALVERSA can cause central serous retinopathy/retinal pigment epithelial detachment (CSR/RPED). Perform monthly ophthalmological examinations during the first four months of treatment, every 3 months afterwards, and at any time for visual symptoms. Withhold BALVERSA when CSR/RPED occurs and permanently discontinue if it does not resolve within 4 weeks or if Grade 4 in severity. (2.3, 5.1)
- Hyperphosphatemia: Increases in phosphate levels are a pharmacodynamic effect of BALVERSA. Monitor for hyperphosphatemia and manage with dose modifications when required. (2.3, 5.2)
- Embryo-fetal toxicity: Can cause fetal harm. Advise patients of the potential risk to the fetus and to use effective contraception (5.3, 8.1, 8.3)

6 ADVERSE REACTIONS

The most common (>20%) adverse reactions, including laboratory abnormalities, were increased phosphate, nail disorders, stomatitis, diarrhea, increased creatinine, increased alkaline phosphatase, increased alanine aminotransferase, decreased hemoglobin, decreased sodium, increased aspartate aminotransferase, fatigue, dry mouth, dry skin, decreased phosphate, decreased appetite, dysgeusia, constipation, increased calcium, dry eye, palmar-plantar erythrodysesthesia syndrome, increased potassium, alopecia, and central serous retinopathy. (6.1)

To report SUSPECTED ADVERSE REACTIONS, contact Janssen Products, LP. at 1-800-526-7736 (1-800-JANSSEN and www.BALVERSA.com) or FDA at 1-800-FDA-1088 or www.fda.gov/medwatch.

7 DRUG INTERACTIONS

- Moderate CYP2C9 or strong CYP3A4 inhibitors: Consider alternative agents or monitor closely for adverse reactions. (7.1)
- Strong CYP3A4 inducers: Avoid concomitant use with BALVERSA. (7.1)
- Moderate CYP3A4 inducers: Administer BALVERSA at a dose of 9 mg. (7.1)
- Serum phosphate level-altering agents: Avoid concomitant use with agents that can alter serum phosphate levels before the initial dose modification period. (2.3, 7.1)
- P-gp substrates: Separate BALVERSA administration by at least 6 hours before or after administration of P-gp substrates with narrow therapeutic indices. (7.2)

8 USE IN SPECIFIC POPULATIONS

- Lactation: Advise not to breastfeed. (8.2)

FULL PRESCRIBING INFORMATION

1 INDICATIONS AND USAGE

BALVERSA is indicated for the treatment of adult patients with locally advanced or metastatic urothelial carcinoma (mUC) with susceptible FGFR3 genetic alterations whose disease has progressed on or after at least one line of prior systemic therapy.

Select patients for therapy based on an FDA-approved companion diagnostic for BALVERSA [see Dosage and Administration (2.1) and Clinical Studies (14.1)] .

Limitations of Use

BALVERSA is not recommended for the treatment of patients who are eligible for and have not received prior PD-1 or PD-L1 inhibitor therapy [see Clinical Studies (14.1)] .

2 DOSAGE AND ADMINISTRATION

2.1 Patient Selection

Select patients for the treatment of locally advanced or metastatic urothelial carcinoma with BALVERSA based on the presence of susceptible FGFR3genetic alterations in tumor specimens as detected by an FDA-approved companion diagnostic [see Clinical Studies (14.1)] .

Information on FDA-approved tests for the detection of FGFR3genetic alterations in urothelial cancer is available at: http://www.fda.gov/CompanionDiagnostics.

2.2 Recommended Dosage and Schedule

The recommended starting dose of BALVERSA is 8 mg (two 4 mg tablets) orally once daily, with a dose increase to 9 mg (three 3 mg tablets) once daily based on tolerability, including hyperphosphatemia, at 14 to 21 days [see Dosage and Administration (2.3)].

Swallow tablets whole with or without food. If vomiting occurs any time after taking BALVERSA, the next dose should be taken the next day. Treatment should continue until disease progression or unacceptable toxicity occurs.

If a dose of BALVERSA is missed, it can be taken as soon as possible on the same day. Resume the regular daily dose schedule for BALVERSA the next day. Extra tablets should not be taken to make up for the missed dose.

Dose Increase based on Serum Phosphate Levels

Assess serum phosphate levels 14 to 21 days after initiating treatment. Increase the dose of BALVERSA to 9 mg once daily if serum phosphate level is < 9.0 mg/dL and there are no ocular disorders or Grade 2 or greater adverse reactions. If the phosphate level is 9.0 mg/dL or higher follow the relevant dose modifications in Table 2. Monitor phosphate levels monthly for hyperphosphatemia [see Pharmacodynamics (12.2)] .

2.3 Dose Modifications for Adverse Reactions

The recommended dose modifications for adverse reactions are listed in Table 1.

Table 1: BALVERSA Dose Reduction Schedule
Dose | 1stdose reduction | 2nddose reduction | 3rddose reduction | 4thdose reduction | 5thdose reduction
9 mg ➞ (three 3 mg tablets) | 8 mg (two 4 mg tablets) | 6 mg (two 3 mg tablets) | 5 mg (one 5 mg tablet) | 4 mg (one 4 mg tablet) | Stop
8 mg ➞ (two 4 mg tablets) | 6 mg (two 3 mg tablets) | 5 mg (one 5 mg tablet) | 4 mg (one 4 mg tablet) | Stop

Table 2 summarizes recommendations for dose interruption, reduction, or discontinuation of BALVERSA in the management of specific adverse reactions.

Table 2: Dose Modifications for Adverse Reactions
Adverse Reaction | BALVERSA Dose Modification
Hyperphosphatemia
In all patients, restrict phosphate intake to 600–800 mg daily.
<6.99 mg/dL | Continue BALVERSA at current dose.
7–8.99 mg/dL | - Continue BALVERSA at current dose. - Start phosphate binder with food until phosphate level is <7 mg/dL. - Reduce the dose if serum phosphate remains ≥7 mg/dL for a period of 2 months or if clinically necessary.
9–10 mg/dL | - Withhold BALVERSA with weekly reassessments until level returns to <7 mg/dL. Then restart BALVERSA at the same dose level. - Start phosphate binder with food until serum phosphate level returns to <7 mg/dL. - Reduce the dose if serum phosphate remains ≥9 mg/dL for a period of 1 month or if clinically necessary.
>10 mg/dL | - Withhold BALVERSA with weekly reassessments until level returns to <7 mg/dL. Then may restart BALVERSA at the first reduced dose level. - If hyperphosphatemia (≥10 mg/dL) for >2 weeks, discontinue BALVERSA permanently. - Medical management of symptoms as clinically relevant.
Serum phosphate with life-threatening consequences; urgent intervention indicated (e.g., dialysis) | - Discontinue BALVERSA permanently.
Central Serous Retinopathy (CSR)
Any | Withhold BALVERSA and perform an ophthalmic evaluation within 2 weeks:; - If improving within 14 days, restart BALVERSA at the current dose. - If not improving within 14 days, withhold BALVERSA until improving; once improving, may resume at the next lower dose level.; Upon restarting BALVERSA, monitor for recurrence every 1 to 2 weeks for a month. If recurs or has not improved after 4 weeks of withholding BALVERSA, consider permanent discontinuation.
Other Adverse Reactions [Dose adjustment graded using the National Cancer Institute Common Terminology Criteria for Adverse Events (NCI CTCAEv5.0).]
Grade 3 | Withhold BALVERSA until resolves to Grade 1 or baseline, then may resume dose level lower.
Grade 4 | Permanently discontinue.

3 DOSAGE FORMS AND STRENGTHS

Tablets:

- 3 mg: Yellow, round biconvex, film-coated, debossed with "3" on one side; and "EF" on the other side.
- 4 mg: Orange, round biconvex, film-coated, debossed with "4" on one side; and "EF" on the other side.
- 5 mg: Brown, round biconvex, film-coated, debossed with "5" on one side; and "EF" on the other side.

4 CONTRAINDICATIONS

None.

5 WARNINGS AND PRECAUTIONS

5.1 Ocular Disorders

BALVERSA can cause ocular disorders, including central serous retinopathy/retinal pigment epithelial detachment (CSR/RPED) resulting in visual field defect.

In the pooled safety population [see Adverse Reactions (6)] , CSR/RPED occurred in 22% of patients treated with BALVERSA, with a median time to first onset of 46 days. In 104 patients with CSR, 40% required dose interruptions and 56% required dose reductions; 2.9% of BALVERSA-treated patients required permanent discontinuation for CSR. Of the 24 patients who restarted BALVERSA after dose interruption with or without dose reduction, 67% had recurrence and/or worsening of CSR after restarting. CSR was ongoing in 41% of the 104 patients at the time of last evaluation.

Dry eye symptoms occurred in 26% of BALVERSA-treated patients. All patients should receive dry eye prophylaxis with ocular demulcents as needed.

Perform monthly ophthalmological examinations during the first 4 months of treatment and every 3 months afterwards, and urgently at any time for visual symptoms. Ophthalmological examination should include assessment of visual acuity, slit lamp examination, fundoscopy, and optical coherence tomography.

Withhold or permanently discontinue BALVERSA based on severity and/or ophthalmology exam findings [see Dosage and Administration (2.3)] .

5.2 Hyperphosphatemia and Soft Tissue Mineralization

BALVERSA can cause hyperphosphatemia leading to soft tissue mineralization, cutaneous calcinosis, non-uremic calciphylaxis and vascular calcification. Increases in phosphate levels are a pharmacodynamic effect of BALVERSA [see Pharmacodynamics (12.2)].

In the pooled safety population [see Adverse Reactions (6)], increased phosphate occurred in 73% of BALVERSA-treated patients. The median onset time of increased phosphate was 16 days (range: 8–421) after initiating BALVERSA. Twenty-four percent of patients received phosphate binders during treatment with BALVERSA. Vascular calcification was observed in 0.2% of patients treated with BALVERSA.

Monitor for hyperphosphatemia throughout treatment. Restrict dietary phosphate intake (600–800 mg daily) and avoid concomitant use of agents that may increase serum phosphate levels.

If serum phosphate is above 7.0 mg/dL, consider adding an oral phosphate binder until serum phosphate level returns to <7.0 mg/dL. Withhold, dose reduce, or permanently discontinue BALVERSA based on duration and severity of hyperphosphatemia according to Table 2 [see Dosage and Administration (2.3)].

5.3 Embryo-Fetal Toxicity

Based on the mechanism of action and findings in animal reproduction studies, BALVERSA can cause fetal harm when administered to a pregnant woman. In an embryo-fetal toxicity study, oral administration of erdafitinib to pregnant rats during the period of organogenesis caused malformations and embryo-fetal death at maternal exposures that were less than the human exposures at the maximum human recommended dose based on area under the curve (AUC). Advise pregnant women of the potential risk to the fetus. Advise female patients of reproductive potential to use effective contraception during treatment with BALVERSA and for one month after the last dose. Advise male patients with female partners of reproductive potential to use effective contraception during treatment with BALVERSA and for one month after the last dose [see Use in Specific Populations (8.1, 8.3)and Clinical Pharmacology (12.1)] .

6 ADVERSE REACTIONS

The following serious adverse reactions are also described elsewhere in the labeling:

- Ocular Disorders [see Warnings and Precautions (5.1)] .
- Hyperphosphatemia [see Warnings and Precautions (5.2)] .

6.1 Clinical Trials Experience

Because clinical trials are conducted under widely varying conditions, adverse reaction rates observed in the clinical trials of a drug cannot be directly compared to rates in the clinical trials of another drug and may not reflect the rates observed in practice.

The pooled safety population described in the WARNINGS AND PRECAUTIONS reflects exposure to BALVERSA as a single agent at the recommended dose (8 to 9 mg orally daily) in 479 patients with advanced urothelial cancer and FGFRalterations in 42756493BLC3001 (NCT03390504), 42756493BLC2001 (NCT02365597), 42756493BLC2002 (NCT 03473743), and 42756493EDI1001 (NCT01703481). Among 479 patients who received BALVERSA, the median duration of treatment was 4.8 months (range: 0.1 to 43 months). In this pooled safety population, the most common (>20%) adverse reactions, including laboratory abnormalities, were increased phosphate, nail disorders, stomatitis, diarrhea, increased creatinine, increased alkaline phosphatase, increased alanine aminotransferase, decreased hemoglobin, decreased sodium, increased aspartate aminotransferase, fatigue, dry mouth, dry skin, decreased phosphate, decreased appetite, dysgeusia, constipation, increased calcium, dry eye, palmar-plantar erythrodysesthesia syndrome, increased potassium, alopecia, and central serous retinopathy.

BLC3001

The safety of BALVERSA was evaluated in Cohort 1 of the BLC3001 study that included patients with locally advanced unresectable or metastatic urothelial carcinoma which had susceptible FGFR3genetic alterations and were previously treated with a PD-1 or PD-L1 inhibitor [see Clinical Studies (14.1)] . Patients received either BALVERSA (8 mg orally once daily with individualized up-titration to 9 mg) (n=135) or chemotherapy (docetaxel 75 mg/m^2once every 3 weeks or vinflunine 320 mg/m^2once every 3 weeks) (n=112). Among patients who received BALVERSA, median duration of treatment was 4.8 months (range: 0.2 to 38 months).

Serious adverse reactions occurred in 41% of patients who received BALVERSA. Serious reactions in >2% of patients included urinary tract infection (4.4%), hematuria (3.7%), hyponatremia (2.2%), and acute kidney injury (2.2%). Fatal adverse reactions occurred in 4.4% of patients who received BALVERSA, including sudden death (1.5%), pneumonia (1.5%), renal failure (0.7%), and cardiorespiratory arrest (0.7%).

Permanent discontinuation of BALVERSA due to an adverse reaction occurred in 14% of patients. Adverse reactions which resulted in permanent discontinuation of BALVERSA in >2% of patients included nail disorders (3%) and eye disorders (2.2%).

Dosage interruptions of BALVERSA due to an adverse reaction occurred in 72% of patients. Adverse reactions which required dosage interruption in >4% of patients included nail disorders (22%), stomatitis (19%), eye disorders (16%), palmar-plantar erythrodysesthesia syndrome (15%), diarrhea (10%), hyperphosphatemia (7%), increased aspartate aminotransferase (6%), and increased alanine aminotransferase (5%).

Dose reductions of BALVERSA due to an adverse reaction occurred in 69% of patients. Adverse reactions which required dose reductions in >4% of patients included nail disorders (27%), stomatitis (19%), eye disorders (17%), palmar-plantar erythrodysesthesia syndrome (12%), diarrhea (7%), dry mouth (4.4%), and hyperphosphatemia (4.4%).

Table 3 presents adverse reactions reported in ≥15% of patients treated with BALVERSA at 8 or 9 mg once daily versus chemotherapy.

Table 3: Adverse Reactions Reported in ≥15% of Patients Who Received BALVERSA Versus Chemotherapy (Study BLC3001)
Adverse Reaction | BALVERSA (N=135) |  | Chemotherapy (N=112)
Adverse Reaction | All Grades (%) | Grade 3–4 (%) | All Grades (%) | Grade 3–4 (%)
Skin and subcutaneous tissue disorders
Nail disorders [Includes multiple terms] | 70 | 12 | 5 | 0
Palmar-plantar erythrodysesthesia syndrome | 30 | 10 | 0.9 | 0
Dry skin | 27 | 1.5 | 6 | 0
Alopecia | 25 | 0.7 | 24 | 0
Gastrointestinal disorders
Diarrhea | 63 | 3 | 17 | 2.7
Stomatitis | 56 | 10 | 18 | 1.8
Dry Mouth | 39 | 0 | 3.6 | 0
Constipation | 27 | 0 | 28 | 1.8
Nervous system disorders
Dysgeusia | 30 | 0.7 | 7 | 0
General disorders
Fatigue | 29 | 1.5 | 42 | 7
Metabolism and nutrition disorders
Decreased appetite | 27 | 3 | 21 | 2.7
Eye disorders
Dry eye | 25 | 0.7 | 3.6 | 0
Central serous retinopathy | 18 | 2.2 | 0 | 0
Investigations
Decreased weight | 22 | 2 | 2.7 | 0

Clinically relevant adverse reactions in <15% of patients who received BALVERSA included nausea (15%), pyrexia (15%), epistaxis (13%), vomiting (10%), and arthralgia (10%).

Table 4 presents laboratory abnormalities reported in ≥15% of patients treated with BALVERSA at 8 or 9 mg once daily versus chemotherapy.

Table 4: Selected Laboratory Abnormalities Reported in ≥15% of Patients Who Received BALVERSA Versus Chemotherapy; Cohort 1 Safety Analysis Set (Study BLC3001)
Laboratory Abnormality | BALVERSA (N=135 [The denominator used to calculate the rate varied from 52 to 131 based on the number of patients with a baseline value and at least one post-treatment value.]) |  | Chemotherapy (N=112 [The denominator used to calculate the rate varied from 11 to 102 based on the number of patients with a baseline value and at least one post-treatment value.])
Laboratory Abnormality | All Grades [Severity graded per NCI CTCAE v4.03.] (%) | Grade 3–4 (%) | All Grades (%) | Grade 3–4 (%)
Chemistry
Increased phosphate | 76 | 5 | 0 | 0
Increased alkaline phosphatase | 54 | 4.7 | 29 | 1
Increased alanine aminotransferase | 46 | 3.8 | 15 | 1
Increased aspartate aminotransferase | 44 | 3.1 | 13 | 0
Decreased sodium | 44 | 16 | 25 | 6
Increased creatinine | 43 | 1.5 | 17 | 0
Decreased phosphate | 34 | 8 | 25 | 3.6
Increased calcium | 27 | 8 | 9 | 0
Increased potassium | 24 | 0 | 21 | 0
Hematology
Decreased hemoglobin | 50 | 12 | 57 | 12
Decreased platelet count | 17 | 1.5 | 18 | 1
Decreased neutrophil count | 16 | 0.8 | 40 | 26

BLC2001

The safety of BALVERSA was evaluated in the BLC2001 study that included 87 patients with locally advanced or metastatic urothelial carcinoma which had susceptible FGFR3and other FGFRalterations, and which progressed during or following at least one line of prior chemotherapy including within 12 months of neoadjuvant or adjuvant chemotherapy [see Clinical Studies (14.1)] . Patients were treated with BALVERSA at 8 mg orally once daily; with a dose increase to 9 mg in patients with phosphate levels <5.5 mg/dL on Day 14 of Cycle 1. Median duration of treatment was 5.3 months (range: 0 to 17 months).

Serious adverse reactions occurred in 41% of patients. The most frequent (>3%) serious adverse reactions were central serous retinopathy (4.6%), urinary tract infection (3.4%), and general physical health deterioration (3.4%).

Fatal adverse reactions occurred in 8% of patients, including acute myocardial infarction (1.1%).

Permanent discontinuation of BALVERSA due to an adverse reaction occurred in 21% of patients. The most frequent (≥ 2%) reasons for permanent discontinuation included central serous retinopathy (4.6%), general physical health deterioration (3.4%), palmar-plantar erythrodysesthesia syndrome (2.3%), acute kidney injury (2.3%), and fatigue (2.3%).

Dosage interruptions of BALVERSA occurred in 68% of patients. The most frequent (≥ 5%) adverse reactions requiring dosage interruption included hyperphosphatemia (24%), stomatitis (17%), nail disorders (16%), central serous retinopathy (9%), palmar-plantar erythro-dysesthesia syndrome (8%), and fatigue (8%).

Dose reductions of BALVERSA occurred in 53% of patients. The most frequent (≥ 5%) adverse reactions for dose reductions included nail disorders (21%), stomatitis (15%), central serous retinopathy (14%), hyperphosphatemia (7%), palmar-plantar erythro-dysesthesia syndrome (7%), fatigue (6%), and blurred vision (6%).

Table 5 presents adverse reactions reported in ≥15% of patients treated with BALVERSA at 8 mg or 9 mg once daily.

Table 5: Adverse Reactions Reported in ≥15% of Patients (Study BLC2001)
Adverse Reaction | BALVERSA 8 mg daily (N=87)
Adverse Reaction | All Grades (%) | Grade 3–4 (%)
Gastrointestinal disorders
Stomatitis [Includes multiple terms] | 62 | 11
Diarrhea | 48 | 4.6
Dry mouth | 45 | 0
Constipation | 28 | 1.1
Nausea | 21 | 1.1
Skin and subcutaneous tissue disorders
Nail disorders | 62 | 14
Dry skin | 37 | 0
Alopecia | 26 | 0
Palmar-plantar erythrodysesthesia syndrome | 26 | 6
General disorders and admin. site conditions
Fatigue , [Includes fatal adverse reactions (n=2)] | 54 | 8
Decreased weight | 16 | 0
Metabolism and nutrition disorders
Decreased appetite | 38 | 0.0
Nervous system disorders
Dysgeusia | 38 | 1.1
Eye disorders
Dry eye | 29 | 1.1
Central serous retinopathy | 28 | 4.6
Blurred vision | 17 | 0
Infections and Infestations
Urinary tract infection | 17 | 6

Clinically relevant adverse reactions in <15% of patients who received BALVERSA included pyrexia (14%), extremity pain (13%), vomiting (13%), and peripheral edema (10%).

Table 6 presents laboratory abnormalities reported in ≥15% of patients treated with BALVERSA at 8 mg or 9 mg once daily.

Table 6: Selected Laboratory Abnormalities Reported in ≥ 15% of Patients
Laboratory Abnormality | BALVERSA 8 mg daily (N=87 [The denominator used to calculate the rate varied from 83 to 86 based on the number of patients with a baseline value and at least one post-treatment value.])
Laboratory Abnormality | All Grades (%) | Grade 3–4 (%)
Chemistry
Increased phosphate | 76 | 1.2
Increased creatinine | 52 | 4.7
Increased alanine aminotransferase | 41 | 1.2
Increased alkaline phosphatase | 41 | 1.2
Decreased sodium | 40 | 16
Decreased magnesium | 31 | 1.2
Increased aspartate aminotransferase | 30 | 0
Decreased phosphate | 24 | 9
Increased calcium | 22 | 3.5
Hematology
Decreased hemoglobin | 35 | 3.5
Decreased platelets | 19 | 1.2
Decreased leukocytes | 17 | 0

7 DRUG INTERACTIONS

7.1 Effect of Other Drugs on BALVERSA

Table 7 summarizes drug interactions that affect the exposure of BALVERSA or serum phosphate level and their clinical management.

Table 7: Drug Interactions that Affect BALVERSA
Moderate CYP2C9 or Strong CYP3A4 Inhibitors
Clinical Impact | - Co-administration of BALVERSA with moderate CYP2C9 or strong CYP3A4 inhibitors increased erdafitinib plasma concentrations [see Clinical Pharmacology (12.3)]. - Increased erdafitinib plasma concentrations may lead to increased drug-related toxicity [see Warnings and Precautions (5)].
Clinical Management | - Consider alternative therapies that are not moderate CYP2C9 or strong CYP3A4 inhibitors during treatment with BALVERSA. - If co-administration of a moderate CYP2C9 or strong CYP3A4 inhibitor is unavoidable, monitor closely for adverse reactions and consider dose modifications accordingly [see Dosage and Administration (2.3)]. If the moderate CYP2C9 or strong CYP3A4 inhibitor is discontinued, resume the BALVERSA dose before dose modifications in the absence of drug-related toxicity.
Strong CYP3A4 Inducers
Clinical Impact | - Co-administration of BALVERSA with strong CYP3A4 inducers decreased erdafitinib plasma concentrations [see Clinical Pharmacology (12.3)]. - Decreased erdafitinib plasma concentrations may lead to decreased activity.
Clinical Management | - Avoid co-administration of strong CYP3A4 inducers with BALVERSA.
Moderate CYP3A4 Inducers
Clinical Impact | - Co-administration of BALVERSA with moderate CYP3A4 inducers may decrease erdafitinib plasma concentrations [see Clinical Pharmacology (12.3)]. - Decreased erdafitinib plasma concentrations may lead to decreased activity.
Clinical Management | - If a moderate CYP3A4 inducer must be co-administered at the start of BALVERSA treatment, administer BALVERSA at a dose of 9 mg daily. - When a moderate CYP3A4 inducer is discontinued, continue BALVERSA at the same dose, in the absence of drug-related toxicity.
Serum Phosphate Level-Altering Agents
Clinical Impact | - Co-administration of BALVERSA with other serum phosphate level-altering agents may increase or decrease serum phosphate levels [see Pharmacodynamics (12.2)]. - Changes in serum phosphate levels due to serum phosphate level-altering agents (other than erdafitinib) may interfere with serum phosphate levels needed for the determination of initial dose increased based on serum phosphate levels [see Dosage and Administration (2.3)].
Clinical Management | - Avoid co-administration of serum phosphate level-altering agents with BALVERSA before initial dose increase period based on serum phosphate levels (Days 14 to 21) [see Dosage and Administration (2.3)].

7.2 Effect of BALVERSA on Other Drugs

Table 8 summarizes the effect of BALVERSA on other drugs and their clinical management.

Table 8: BALVERSA Drug Interactions that Affect Other Drugs
P-glycoprotein (P-gp) Substrates
Clinical Impact | - Co-administration of BALVERSA with P-gp substrates may increase the plasma concentrations of P-gp substrates [see Clinical Pharmacology (12.3)]. - Increased plasma concentrations of P-gp substrates may lead to increased toxicity of the P-gp substrates.
Clinical Management | - If co-administration of BALVERSA with P-gp substrates is unavoidable, separate BALVERSA administration by at least 6 hours before or after administration of P-gp substrates with narrow therapeutic index.

8 USE IN SPECIFIC POPULATIONS

8.1 Pregnancy

Risk Summary

Based on the mechanism of action and findings in animal reproduction studies, BALVERSA can cause fetal harm when administered to a pregnant woman [see Clinical Pharmacology (12.1)] . There are no available data on BALVERSA use in pregnant women to inform a drug-associated risk. Oral administration of erdafitinib to pregnant rats during organogenesis caused malformations and embryo-fetal death at maternal exposures that were less than the human exposures at the maximum recommended human dose based on AUC (see Data) . Advise pregnant women and females of reproductive potential of the potential risk to the fetus.

The estimated background risk of major birth defects and miscarriage for the indicated population is unknown. All pregnancies have a background risk of birth defect, loss, or other adverse outcomes. In the U.S. general population, the estimated background risk of major birth defects and miscarriage in clinically recognized pregnancies is 2–4% and 15–20%, respectively.

Data

Animal Data

In an embryo-fetal toxicity study, erdafitinib was orally administered to pregnant rats during the period of organogenesis. Doses ≥4 mg/kg/day (at total maternal exposures <0.1% of total human exposures at the maximum recommended human dose based on AUC) produced embryo-fetal death, major blood vessel malformations and other vascular anomalies, limb malformations (ectrodactyly, absent or misshapen long bones), an increased incidence of skeletal anomalies in multiple bones (vertebrae, sternebrae, ribs), and decreased fetal weight.

8.2 Lactation

Risk Summary

There are no data on the presence of erdafitinib in human milk, or the effects of erdafitinib on the breastfed child, or on milk production. Because of the potential for serious adverse reactions from erdafitinib in a breastfed child, advise lactating women not to breastfeed during treatment with BALVERSA and for one month following the last dose.

8.3 Females and Males of Reproductive Potential

BALVERSA can cause fetal harm when administered to a pregnant woman [see Use in Specific Populations (8.1)] .

Pregnancy Testing

Verify pregnancy status in females of reproductive potential prior to initiating treatment with BALVERSA.

Contraception

Females

Advise females of reproductive potential to use effective contraception during treatment with BALVERSA and for one month after the last dose.

Males

Advise male patients with female partners of reproductive potential to use effective contraception during treatment with BALVERSA and for one month after the last dose.

Infertility

Females

Based on findings from animal studies, BALVERSA may impair fertility in females of reproductive potential [see Nonclinical Toxicology (13.1)] .

8.4 Pediatric Use

Safety and effectiveness of BALVERSA in pediatric patients have not been established.

Skeletal adverse reactions have occurred in pediatric patients treated with BALVERSA. In a study of BALVERSA that included pediatric patients ages 6 to <18 years with FGFR-positive advanced solid tumors, epiphysiolysis and bone fractures occurred.

In the postmarket setting and in literature reports, cases of slipped capital femoral epiphysis and accelerated linear growth in patients treated with BALVERSA have been reported.

Juvenile Animal Toxicity Data

In 4 and 13-week repeat-dose toxicology studies in rats and dogs, toxicities in bone and teeth were observed at an exposure less than the human exposure (AUC) at the maximum recommended human dose. Chondroid dysplasia/metaplasia were reported in multiple bones in both species, and tooth abnormalities included abnormal/irregular denting in rats and dogs and discoloration and degeneration of odontoblasts in rats.

8.5 Geriatric Use

Of the 479 patients treated with BALVERSA in clinical studies, 40% of patients were less than 65 years old, 40% of patients were 65 years to 74 years old, and 20% were 75 years old and over.

Patients 65 years of age and older treated with BALVERSA experienced a higher incidence of adverse reactions requiring treatment discontinuation than younger patients. In clinical trials, the incidence of treatment discontinuations of BALVERSA due to adverse reactions was 10% in patients younger than 65 years, 20% in patients ages 65–74 years, and 35% in patients 75 years or older.

No overall difference in efficacy was observed between these patients and younger patients [see Clinical Studies (14.1)].

8.6 CYP2C9 Poor Metabolizers

CYP2C9*3/*3 Genotype:Erdafitinib plasma concentrations are predicted to be higher in patients with the CYP2C9*3/*3 genotype. Monitor for increased adverse reactions in patients who are known or suspected to have CYP2C9*3/*3 genotype [see Pharmacogenomics (12.5)] .

11 DESCRIPTION

Erdafitinib, the active ingredient in BALVERSA, is a kinase inhibitor. The chemical name is N-(3,5-dimethoxyphenyl)-N'-(1-methylethyl)-N-[3-(1-methyl-1H-pyrazol-4-yl)quinoxalin-6-yl]ethane-1,2-diamine. Erdafitinib is a yellow powder. It is practically insoluble, or insoluble to freely soluble in organic solvents, and slightly soluble to practically insoluble, or insoluble in aqueous media over a wide range of pH values. The molecular formula is C25H30N6O2and molecular weight is 446.56.

Chemical structure of erdafitinib is as follows:

BALVERSA®(erdafitinib) tablets are supplied as 3 mg, 4 mg or 5 mg film-coated tablets for oral administration and contains the following inactive ingredients:

Tablet Core: Croscarmellose sodium, Magnesium stearate (from vegetable source), Mannitol, Meglumine, and Microcrystalline Cellulose.

Film Coating: (Opadry amb II): Glycerol monocaprylocaprate Type I, Polyvinyl alcohol-partially hydrolyzed, Sodium lauryl sulfate, Talc, Titanium dioxide, Iron oxide yellow, Iron oxide red (for the orange and brown tablets only), Ferrosoferric oxide/iron oxide black (for the brown tablets only).

12 CLINICAL PHARMACOLOGY

12.1 Mechanism of Action

Erdafitinib is a kinase inhibitor that binds to and inhibits enzymatic activity of FGFR1, FGFR2, FGFR3 and FGFR4 based on in vitro data. Erdafitinib inhibited FGFR phosphorylation and signaling and decreased cell viability in cell lines expressing FGFR genetic alterations, including point mutations, amplifications, and fusions. Erdafitinib demonstrated antitumor activity in FGFR-expressing cell lines and xenograft models derived from tumor types, including bladder cancer.

12.2 Pharmacodynamics

Cardiac Electrophysiology

Based on evaluation of QTc interval in an open-label, dose escalation and dose expansion study in 187 patients with cancer, erdafitinib had no large effect (i.e., > 20 ms) on the QTc interval.

Serum Phosphate

FGFR inhibition by BALVERSA increases serum phosphate level [see Dosage and Administration (2.3)and Drug Interactions (7.1)].

12.3 Pharmacokinetics

Following administration of BALVERSA 8 mg once daily, the mean (coefficient of variation [CV%]) erdafitinib steady-state maximum plasma concentration (Cmax), area under the curve (AUCtau), and minimum plasma concentration (Cmin) were 1,399 ng/mL (51%), 29,268 ng∙h/mL (60%), and 936 ng/mL (65%), respectively.

Following single and repeat once daily dosing of BALVERSA, erdafitinib exposure (Cmaxand AUC) increased proportionally across the dose range of 0.5 to 12 mg (0.06 to 1.3 times the maximum approved recommended dose). Steady state was achieved after 2 weeks with once daily dosing with a mean accumulation ratio was 4-fold.

Absorption

Median time to achieve peak plasma concentration (tmax) was 2.5 hours (range: 2 to 6 hours).

Effect of Food

No clinically meaningful differences in erdafitinib exposure was observed following administration of BALVERSA with a high-fat and high-calorie meal (800 calories to 1,000 calories with approximately 50% of total caloric content of the meal from fat).

Distribution

The mean apparent volume of distribution of erdafitinib was 29 L.

Erdafitinib protein binding was 99.7% in patients, primarily to alpha-1-acid glycoprotein.

Elimination

The mean total apparent clearance (CL/F) of erdafitinib was 0.362 L/h.

The mean effective half-life of erdafitinib was 59 hours.

Metabolism

Erdafitinib is primarily metabolized by CYP2C9 and CYP3A4. The contribution of CYP2C9 and CYP3A4 in the total clearance of erdafitinib is estimated to be 39% and 20%, respectively. Unchanged erdafitinib was the major drug-related moiety in plasma, there were no circulating metabolites.

Excretion

Following a single oral dose of radiolabeled erdafitinib, approximately 69% of the dose was recovered in feces (19% as unchanged) and 19% in urine (13% as unchanged).

Specific Populations

No clinically meaningful effects on erdafitinib exposure were observed based on age (21–92 years), sex, race (White, Hispanic or Asian), body weight (36–166 kg), mild (Child-Pugh A) or moderate (Child-Pugh B) hepatic impairment, or mild to moderate renal impairment (eGFR 30 to 89 mL/min/1.73 m²). Limited data are available in patients with severe (Child-Pugh C) hepatic impairment and in patients with severe renal impairment. The pharmacokinetics of erdafitinib in patients with renal impairment requiring dialysis is unknown.

Drug Interaction Studies

Clinical Studies

Effect of Other Drugs on Erdafitinib

Moderate CYP2C9 Inhibitors

Erdafitinib mean ratios for Cmaxand AUCinfwere 121% and 148%, respectively, when BALVERSA was co-administered with fluconazole, a moderate CYP2C9 and CYP3A4 inhibitor, relative to BALVERSA administered alone.

Strong CYP3A4 Inhibitors

Erdafitinib mean ratios for Cmaxand AUCinfwere 105% and 134%, respectively, when BALVERSA was co-administered with itraconazole (a strong CYP3A4 inhibitor and P-gp inhibitor) relative to BALVERSA alone.

CYP3A4/2C9 Inducers

Erdafitinib mean ratios for Cmaxand AUCinfwere 78% and 45%, respectively, when BALVERSA was co-administered with carbamazepine (a strong CYP3A4 and weak CYP2C9 inducer) relative to BALVERSA alone.

Effect of Erdafitinib on Other Drugs

CYP3A4 Substrates:

No clinically meaningful effect on the exposure of midazolam (a CYP3A4 substrate) was observed following coadministration with BALVERSA.

OCT2 Substrates:

No clinically meaningful effect on the exposure of metformin (an OCT2 substrate) was observed following coadministration with BALVERSA.

In Vitro Studies

CYP Substrates

Erdafitinib is a time dependent inhibitor and inducer of CYP3A4. Erdafitinib is not an inhibitor of other major CYP isozymes at clinically relevant concentrations.

Transporters

Erdafitinib is a substrate and inhibitor of P-gp. P-gp inhibitors are not expected to affect erdafitinib exposure to a clinically relevant extent. Erdafitinib is an inhibitor of OCT2.

Erdafitinib does not inhibit BCRP, OATP1B, OATP1B3, OAT1, OAT3, OCT1, MATE-1, or MATE-2K at clinically relevant concentrations.

Acid-Lowering Agents

Erdafitinib has adequate solubility across the pH range of 1 to 7.4. Acid-lowering agents (including antacids, H2-antagonists and proton pump inhibitors) are not expected to affect the bioavailability of erdafitinib.

12.5 Pharmacogenomics

CYP2C9 activity is reduced in individuals with genetic variants, such as the CYP2C9*2 and CYP2C9*3 polymorphisms. Erdafitinib exposure was similar in subjects with CYP2C9*1/*2 and *1/*3 genotypes relative to subjects with CYP2C9*1/*1 genotype (wild type). No data are available in subjects characterized by other genotypes (e.g., *2/*2, *2/*3, *3/*3). Simulation suggested no clinically meaningful differences in erdafitinib exposure in subjects with CYP2C9*2/*2 and *2/*3 genotypes. The exposure of erdafitinib is predicted to be 50% higher in subjects with the CYP2C9*3/*3 genotype, estimated to be present in 0.4% to 3% of the population among various ethnic groups.

13 NONCLINICAL TOXICOLOGY

13.1 Carcinogenesis, Mutagenesis, and Impairment of Fertility

Carcinogenicity studies have not been conducted with erdafitinib.

Erdafitinib was not mutagenic in a bacterial reverse mutation (Ames) assay and was not clastogenic in an in vitro micronucleus or an in vivo rat bone marrow micronucleus assay.

Fertility studies in animals have not been conducted with erdafitinib. In the 3-month repeat-dose toxicity study, erdafitinib showed effects on female reproductive organs (necrosis of the ovarian corpora lutea) in rats at an exposure less than the human exposure (AUC) at maximum recommended human dose.

14 CLINICAL STUDIES

14.1 Urothelial Carcinoma with Susceptible FGFR3Genetic Alterations

The efficacy of BALVERSA was evaluated in Study BLC3001 (NCT03390504) Cohort 1, a randomized, open-label, multicenter study in which 266 patients with advanced urothelial cancer harboring selected FGFR3alterations were randomized 1:1 to receive BALVERSA (8 mg with titration up to 9 mg) versus chemotherapy (docetaxel 75 mg/m^2once every 3 weeks or vinflunine 320 mg/m^2once every 3 weeks) until unacceptable toxicity or progression. Randomization was stratified by region (North America vs. Europe vs. rest of world), Eastern Cooperative Oncology Group (ECOG) performance status (0 or 1 vs. 2) and visceral or bone metastases (yes vs. no). All patients needed to have had disease progression after 1 or 2 prior treatments, at least 1 of which included a PD-1 or PD-L1 inhibitor. FGFR3genetic alterations were identified from tumor tissue in a central laboratory by the QIAGEN therascreen® FGFRRGQ RT-Polymerase Chain Reaction (PCR) kit in 75% of patients while the remainder (25%) were identified by local next generation sequencing (NGS) assays.

The major efficacy outcome measures were overall survival (OS), progression-free survival (PFS), and objective response rate (ORR) assessed by investigator using RECIST (Response Evaluation Criteria in Solid Tumors) Version 1.1.

The median age was 67 years (range: 32 to 86 years) and 71% were male; 54% were White, 29% Asian, 0.4% Black, 0.4% multiple races, 16% not reported; 2% were Hispanic/Latino; and baseline ECOG performance status was 0 (43%), 1 (48%), or 2 (9%). Eighty-one percent of patients had FGFR3mutations, 17% had fusions, and 2% had both mutations and fusions. Ninety-five percent of patients had pure transitional cell carcinoma (TCC) and 5% had TCC with other histologic variants. The primary tumor location was the upper tract for 33% of subjects and lower tract for 67%; 74% of patients had visceral or bone metastases. Eighty-eight percent of patients received platinum-containing chemotherapy previously. PD-1 or PD-L1 inhibitor therapy was received only in the neoadjuvant or adjuvant setting in 7% of patients.

Statistically significant improvements in OS, PFS, and ORR were demonstrated for BALVERSA compared with chemotherapy.

Table 9 and Figures 1 and 2 summarize the efficacy results for BLC3001 Cohort 1.

Table 9: Efficacy Results for Study BLC3001 Cohort 1
 | BALVERSA N=136 | Chemotherapy N=130
Overall Survival (OS)
Number of events (%) | 77 (56.6%) | 78 (60.0%)
Median [Based on Kaplan-Meier estimates] , months (95% CI) | 12.1 (10.3, 16.4) | 7.8 (6.5, 11.1)
Hazard ratio [Based on an unstratified Cox proportional hazard model] (95% CI) | 0.64 (0.47, 0.88)
p-value [Based on an unstratified log-rank test] | 0.0050
Progression-free survival (PFS)
Number of events (%) | 101 (74.3%) | 90 (69.2%)
Median , months (95% CI) | 5.6 (4.4, 5.7) | 2.7 (1.8, 3.7)
Hazard ratio (95% CI) | 0.58 (0.44, 0.78)
p-value | 0.0002
Objective response rate (ORR)
ORR (95% CI) | 35.3% (27.3, 43.9) | 8.5% (4.3, 14.6)
p-value [p-value is estimated using Cochran-Haenszel (CMH) test with ECOG performance status (0 or 1 vs 2) as a stratification factor.] | <0.001
Complete response, CR (%) | 5.1% | 0.8%
Partial response, PR (%) | 30.1% | 7.7%
All p-values reported are 2-sided and compared with 0.019 of the allocated alpha for the interim analysis.
ORR = confirmed objective response (CR + PR)
CI = Confidence Interval

Figure 1: Kaplan-Meier Plot of Overall Survival (Study BLC3001 Cohort 1)

Figure 2: Kaplan-Meier Plot of Progression-free Survival (Study BLC3001 Cohort 1)

Study BLC3001 Cohort 2

Study BLC3001 (NCT03390504) Cohort 2 was a multicenter, open-label, randomized study in 351 patients with locally advanced or metastatic urothelial carcinoma with selected FGFR3alterations who received 1 prior line of systemic therapy and no prior PD-1 or PD-L1 inhibitor. Patients were randomized 1:1 to receive BALVERSA (8 mg with titration up to 9 mg) or pembrolizumab 200 mg every 3 weeks. The study did not meet its major efficacy outcome measure for superiority of OS at the pre-specified final analysis. The OS hazard ratio (HR) was 1.18 (95% CI: 0.92, 1.51; p=0.18), median 10.9 (95% CI: 9.2, 12.6) months for BALVERSA versus 11.1 (95% CI: 9.7, 13.6) months for pembrolizumab [see Indications and Usage (1)] .

Study BLC2001

Study BLC2001 (NCT02365597) was a multicenter, open-label, single-arm study to evaluate the efficacy and safety of BALVERSA in patients with locally advanced or metastatic urothelial carcinoma (mUC). FGFRmutation status for screening and enrollment of patients was determined by a clinical trial assay (CTA). The efficacy population consists of a cohort of eighty-seven patients who were enrolled in this study with disease that had progressed on or after at least one prior chemotherapy and that had at least 1 of the following genetic alterations: FGFR3gene mutations (R248C, S249C, G370C, Y373C) or FGFRgene fusions (FGFR3-TACC3, FGFR3-BAIAP2L1, FGFR2-BICC1, FGFR2-CASP7), as determined by the CTA performed at a central laboratory. Tumor samples from 69 patients were tested retrospectively by the QIAGEN therascreen® FGFRRGQ RT-PCR Kit, which is the FDA-approved test for selection of patients with mUC for BALVERSA.

Patients received a starting dose of BALVERSA at 8 mg once daily with a dose increase to 9 mg once daily in patients whose serum phosphate levels were below the target of 5.5 mg/dL between days 14 and 17; a dose increase occurred in 41% of patients. BALVERSA was administered until disease progression or unacceptable toxicity. The major efficacy outcome measures were ORR and duration of response (DoR), as determined by blinded independent review committee (BIRC) according to RECIST v1.1.

The median age was 67 years (range: 36 to 87 years), 79% were male, and 74% were Caucasian. Most patients (92%) had a baseline Eastern Cooperative Oncology Group (ECOG) performance status of 0 or 1. Sixty-six percent of patients had visceral metastases. Eighty-four (97%) patients received at least one of cisplatin or carboplatin previously. Fifty-six percent of patients only received prior cisplatin-based regimens, 29% received only prior carboplatin-based regimens, and 10% received both cisplatin and carboplatin-based regimens. Three (3%) patients had disease progression following prior platinum-containing neoadjuvant or adjuvant therapy only. Twenty-four percent of patients had been treated with prior anti PD-L1/PD-1 therapy.

Efficacy results are summarized in Table 10 and Table 11. ORR was 32.2%. Responders included patients who had previously not responded to anti PD-L1/PD-1 therapy.

Table 10: Efficacy Results
Endpoint | BIRC [BIRC: Blinded Independent Review Committee] Assessment
Endpoint | N=87
ORR (95% CI) | 32.2% (22.4, 42.0)
Complete response (CR) | 2.3%
Partial response (PR) | 29.9%
Median DoR in months (95% CI) | 5.4 (4.2, 6.9)
ORR = CR + PR
CI = Confidence Interval

Table 11: Efficacy Results by FGFR Genetic Alteration
 | BIRC [BIRC: Blinded Independent Review Committee] Assessment
FGFR3Point Mutation | N=64
ORR (95% CI) | 40.6% (28.6, 52.7)
FGFR3Fusion [Both responders had FGFR3-TACC3_V1 fusion] , [One patient with a FGFR2-CASP7/FGFR3-TACC3_V3 fusion is reported in both FGFR2 fusion and FGFR3 fusion above] | N=18
ORR (95% CI) | 11.1% (0, 25.6)
FGFR2Fusion | N=6
ORR | 0
ORR = CR + PR
CI = Confidence Interval

16 HOW SUPPLIED/STORAGE AND HANDLING

BALVERSA®(erdafitinib) tablets are available in the strengths and packages listed below:

- 3 mg tablets: Yellow, round biconvex, film-coated, debossed with "3" on one side and "EF" on the other side.
  - Bottle of 56-tablets with child resistant closure (NDC 59676-030-56).
  - Bottle of 84-tablets with child resistant closure (NDC 59676-030-84).
- 4 mg tablets: Orange, round biconvex, film-coated, debossed with "4" on one side and "EF" on the other side.
  - Bottle of 28-tablets with child resistant closure (NDC 59676-040-28).
  - Bottle of 56-tablets with child resistant closure (NDC 59676-040-56).
- 5 mg tablets: Brown, round biconvex, film-coated, debossed with "5" on one side and "EF" on the other side.
  - Bottle of 28-tablets with child resistant closure (NDC 59676-050-28).

STORAGE AND HANDLING

Store at 20 °C to 25 °C (68 °F to 77 °F); excursions permitted between 15 °C to 30 °C (59 °F to 86 °F) [see USP Controlled Room Temperature].

17 PATIENT COUNSELING INFORMATION

Advise the patient to read the FDA-approved patient labeling (Patient Information).

FGFRGenetic Alterations

Advise patients that evidence of a susceptible FGFR3mutation or gene fusion within the tumor specimen is necessary to identify patients for whom treatment is indicated [see Dosage and Administration (2.1)] .

Ocular Disorders

Advise patients to contact their healthcare provider if they experience any visual changes [see Warnings and Precautions (5.1)]. In order to prevent or treat dry eyes, advise patients to use artificial tear substitutes, hydrating or lubricating eye gels or ointments frequently, at least every 2 hours during waking hours [see Dosage and Administration (2.3)].

Skin, Mucous or Nail Disorders

Advise patients to contact their healthcare provider if they experience progressive or intolerable skin, mucous or nail disorders [see Adverse Reactions (6.1)] .

Hyperphosphatemia and Soft Tissue Mineralization

Inform patients that BALVERSA may cause hyperphosphatemia and soft tissue mineralization. Advise patients to immediately inform their healthcare provider of painful skin lesions or any symptoms related to acute change in phosphate levels such as muscle cramps, numbness, or tingling around the mouth [see Warnings and Precautions (5.2)] .

Advise patients that their healthcare provider will assess their serum phosphate level between 14 and 21 days of initiating treatment and will adjust the dose if needed [see Warnings and Precautions (5.2)] . Advise patients to restrict phosphate intake to 600–800 mg daily. During this initial phosphate-assessment period, advise patients to avoid concomitant use with agents that can alter serum phosphate levels. Advise patients that, after the initial phosphate assessment period, monthly phosphate level monitoring for hyperphosphatemia should be performed during treatment with BALVERSA [see Drug Interactions (7.1)].

Drug Interactions

Advise patients to inform their healthcare providers of all concomitant medications, including prescription medicines, over-the-counter drugs, and herbal products [see Drug Interactions (7.1, 7.2)] .

Dosing Instructions

Instruct patients to swallow the tablets whole once daily with or without food. If vomiting occurs any time after taking BALVERSA, advise patients to take the next dose the next day [see Dosage and Administration (2.2)] .

Missed Dose

If a dose is missed, advise patients to take the missed dose as soon as possible. Resume the regular daily dose schedule for BALVERSA the next day. Extra tablets should not be taken to make up for the missed dose [see Dosage and Administration (2.3)] .

Embryo-Fetal Toxicity

Advise pregnant women and females of reproductive potential of the potential risk to the fetus. Advise females to inform their healthcare providers of a known or suspected pregnancy [see Warnings and Precautions (5.3)and Use in Specific Populations (8.1)] .

Advise female patients of reproductive potential to use effective contraception during treatment and for one month after the last dose of BALVERSA. Advise male patients with female partners of reproductive potential to use effective contraception during treatment and for one month after the last dose of BALVERSA [see Use in Specific Populations (8.3)].

Lactation

Advise females not to breastfeed during treatment with BALVERSA and for one month after the last dose [see Use in Specific Populations (8.2)].

Infertility

Advise females of reproductive potential that BALVERSA may impair fertility [see Use in Specific Populations (8.3)].

Product of Switzerland

Manufactured for:
Janssen Products, LP
Horsham, PA 19044, USA

Under license from Astex Therapeutics Limited.

For patent information: www.janssenpatents.com

©2019 Janssen Pharmaceutical Companies

PATIENT INFORMATION
BALVERSA®(bal-VER-sah)
(erdafitinib) tablets

What is BALVERSA?
BALVERSA is a prescription medicine used to treat adults with bladder cancer (urothelial cancer) that has spread or cannot be removed by surgery:

- which has a certain type of abnormal FGFR gene, and
- who have tried at least one other medicine by mouth or injection (systemic therapy) that did not work or is no longer working.

Your healthcare provider will test your cancer for certain types of abnormal FGFR genes and make sure that BALVERSA is right for you.
BALVERSA is not recommended for the treatment of people who are eligible for and have not received prior PD-1 or PD-L1 inhibitor therapy.
It is not known if BALVERSA is safe and effective in children.

Before taking BALVERSA tell your healthcare provider about all of your medical conditions, including if you:

- have vision or eye problems.
- are pregnant or plan to become pregnant. BALVERSA can harm your unborn baby. You should not become pregnant during treatment with BALVERSA.
  Females who can become pregnant:
  - Your healthcare provider may do a pregnancy test before you start treatment with BALVERSA.
  - You should use effective birth control during treatment and for 1 month after the last dose of BALVERSA. Talk to your healthcare provider about birth control methods that may be right for you.
  - Tell your healthcare provider right away if you become pregnant or think you may be pregnant.
  Males with female partners who can become pregnant:
  - You should use effective birth control when sexually active during treatment with BALVERSA and for 1 month after the last dose.
- are breastfeeding or plan to breastfeed. Do not breastfeed during treatment and for 1 month after the last dose of BALVERSA.

Tell your healthcare provider about all the medicines you take, including prescription and over-the-counter medicines, vitamins, and herbal supplements.

How should I take BALVERSA?

- Take BALVERSA exactly as your healthcare provider tells you.
- Take BALVERSA 1 time each day.
- Swallow BALVERSA tablets whole with or without food.
- Your healthcare provider may change your dose of BALVERSA, temporarily stop or completely stop treatment if you get certain side effects.
- If you miss a dose of BALVERSA, take the missed dose as soon as possible on the same day. Take your regular dose of BALVERSA the next day. Do not take more BALVERSA than prescribed to make up for the missed dose.
- If you vomit after taking BALVERSA, do not take another BALVERSA tablet. Take your regular dose of BALVERSA the next day.

What are the possible side effects of BALVERSA?
BALVERSA may cause serious side effects, including:

- Eye problems.Eye problems are common with BALVERSA but can also be serious. Eye problems include dry or inflamed eyes, inflamed cornea (front part of the eye) and disorders of the retina, an internal part of the eye. Tell your healthcare provider right away if you develop blurred vision, loss of vision or other visual changes. You should use artificial tear substitutes, hydrating or lubricating eye gels or ointments at least every 2 hours during waking hours to help prevent dry eyes. During treatment with BALVERSA, your healthcare provider will send you to see an eye specialist.
- High phosphate levels in the blood (hyperphosphatemia).Hyperphosphatemia is common with BALVERSA but can also be serious. High levels of phosphate in your blood may lead to build-up of minerals such as calcium in different tissues in your body. Your healthcare provider will check your blood phosphate level between 14 and 21 days after starting treatment with BALVERSA, and then monthly.
  - Your healthcare provider may prescribe changes in your diet or phosphate lowering therapy, or change or stop treatment with BALVERSA if needed.
  - Tell your healthcare provider right away if you develop painful skin lesions, any muscle cramps, or numbness or tingling around your mouth.

The most common side effects of BALVERSA include:

- nails separate from the bed or poor formation of the nail
- mouth sores
- diarrhea
- increased level of creatinine in the blood
- increased level of the enzyme alkaline phosphatase in the blood
- change in liver function
- decreased red blood cells (anemia)
- decreased salt (sodium) levels in the blood
- tiredness
- dry mouth

- dry skin
- decreased phosphate in the blood
- decreased appetite
- change in sense of taste
- constipation
- increased level of calcium in the blood
- dry eye
- redness, swelling, peeling or tenderness, mainly on the hands or feet (hand-foot syndrome)
- increased level of potassium in the blood
- hair loss
- fluid buildup behind the retina in your eye

Tell your healthcare provider right away if you develop any nail or skin problems including nails separating from the nail bed, nail pain, nail bleeding, breaking of the nails, color or texture changes in your nails, infected skin around the nail, an itchy skin rash, dry skin, or cracks in the skin.
BALVERSA may affect fertility in females who are able to become pregnant. Talk to your healthcare provider if this is a concern for you.
These are not all of the possible side effects of BALVERSA. Call your healthcare provider for medical advice about side effects. You may report side effects to FDA at 1-800-FDA-1088.

How should I store BALVERSA?

- Store BALVERSA tablets at room temperature between 68 °F to 77 °F (20 °C to 25 °C).

Keep BALVERSA and all medicines out of the reach of children.

General information about the safe and effective use of BALVERSA.
Medicines are sometimes prescribed for purposes other than those listed in Patient Information leaflets. Do not use BALVERSA for a condition for which it was not prescribed. Do not give BALVERSA to other people, even if they have the same symptoms that you have. It may harm them. If you would like more information, talk with your healthcare provider. You can ask your pharmacist or healthcare provider for information about BALVERSA that is written for healthcare professionals.

What are the ingredients in BALVERSA?
Active ingredient:erdafitinib
Inactive ingredients:
Tablet Core: Croscarmellose sodium, Magnesium stearate (from vegetable source), Mannitol, Meglumine, and Microcrystalline Cellulose.
Film Coating (Opadry amb II): Glycerol monocaprylocaprate Type I, Polyvinyl alcohol-partially hydrolyzed, Sodium lauryl sulfate, Talc, Titanium dioxide, Iron oxide yellow, Iron oxide red (for the orange and brown tablets only), Ferrosoferric oxide/iron oxide black (for the brown tablets only).
Manufactured for:Janssen Products, LP, Horsham, PA 19044, USA
For patent information: www.janssenpatents.com
© 2019 Janssen Pharmaceutical Companies
For more information call Janssen Products, LP at 1-800-526-7736 (1-800-JANSSEN) or go to www.BALVERSA.com.

This Patient Information has been approved by the U.S. Food and Drug Administration.

Revised: 10/2024

PRINCIPAL DISPLAY PANEL - 3 mg Tablet Bottle Carton

NDC 59676-030-56

Balversa®
(erdafitinib) tablets

3 mg

Each film-coated tablet
contains 3 mg of erdafitinib.

Rx only

56 film-coated tablets

PRINCIPAL DISPLAY PANEL - 4 mg Tablet Bottle Carton

NDC 59676-040-56

Balversa®
(erdafitinib) tablets

4 mg

Each film-coated tablet
contains 4 mg of erdafitinib.

Rx only

56 film-coated tablets

PRINCIPAL DISPLAY PANEL - 5 mg Tablet Bottle Carton

NDC 59676-050-28

Balversa®
(erdafitinib) tablets

5 mg

Each film-coated tablet
contains 5 mg of erdafitinib.

Rx only

28 film-coated tablets